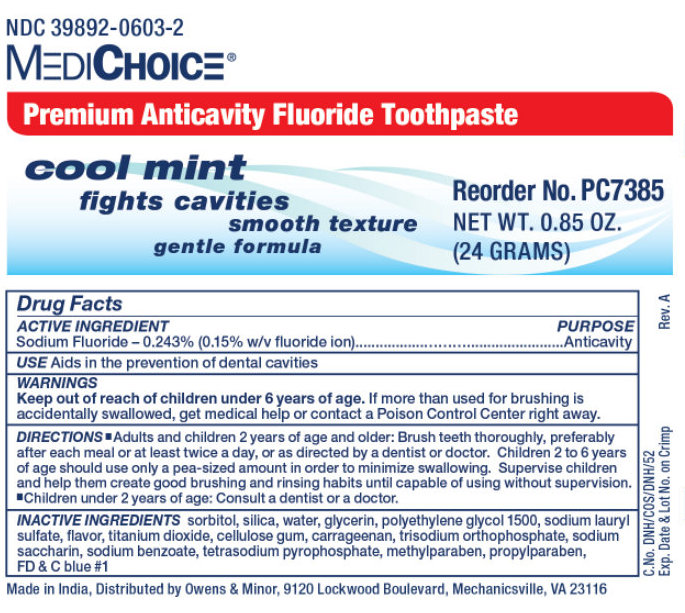 DRUG LABEL: MediChoice Premium Anticavity Fluoride
NDC: 39892-0603 | Form: PASTE, DENTIFRICE
Manufacturer: O&M HALYARD, INC.
Category: otc | Type: HUMAN OTC DRUG LABEL
Date: 20251008

ACTIVE INGREDIENTS: SODIUM FLUORIDE 2.43 mg/1 g
INACTIVE INGREDIENTS: SORBITOL; SILICON DIOXIDE; WATER; GLYCERIN; POLYETHYLENE GLYCOL 1500; SODIUM LAURYL SULFATE; TITANIUM DIOXIDE; CARBOXYMETHYLCELLULOSE SODIUM; CARRAGEENAN; SODIUM PHOSPHATE, TRIBASIC, DODECAHYDRATE; SACCHARIN SODIUM; SODIUM BENZOATE; SODIUM PYROPHOSPHATE; METHYLPARABEN; PROPYLPARABEN; FD&C BLUE NO. 1

MediChoice Premium Anticavity Fluoride Toothpaste

MediChoice Premium Anticavity Fluoride Toothpaste

Drug Facts

ACTIVE INGREDIENT

Sodium Fluoride - 0.243% (0.15% w/v fluoride ion)

PURPOSE

Anticavity

USE

Aids in the prevention of dental cavities

WARNINGS

KEEP OUT OF REACH OF CHILDREN

If more than used for brushing is accidentally swallowed, get medical help or contact a Poison Control Center right away. Keep out of reach of children under 6 years of age.

DIRECTIONS

- Adults and children 2 years of age and olden Brush teeth thoroughly, preferably after each meal or at least twice a day, or as directed by a dentist or doctor. Children 2 to 6 years of age should use only a pea-sized amount in order to minimize swallowing. Supervise children and help them create good brushing and rinsing habits until capable of using without supervision.
- Children under 2 years of age: Consult a dentist or a doctor.

INACTIVE INGREDIENTS

sorbitol, silica, water, glycerin, polythelene glycol 1500, sodium lauryl sulfate, flavor, titanium dioxide, cellulose gum, carrageenan, trisodium orthophosphate, sodium saccharin, sodium benzoate, tetrasodium pyrophosphate, methylparaben, propylparaben, FD & C blue #1

Made in India, Distributed by Owens & Minor, 9120 Lockwood Boulevard, Mechanicsville, VA 23116

C.No. DNH/COS/DNH/52Exp. Date & Lot No. on Crimp Rev. A